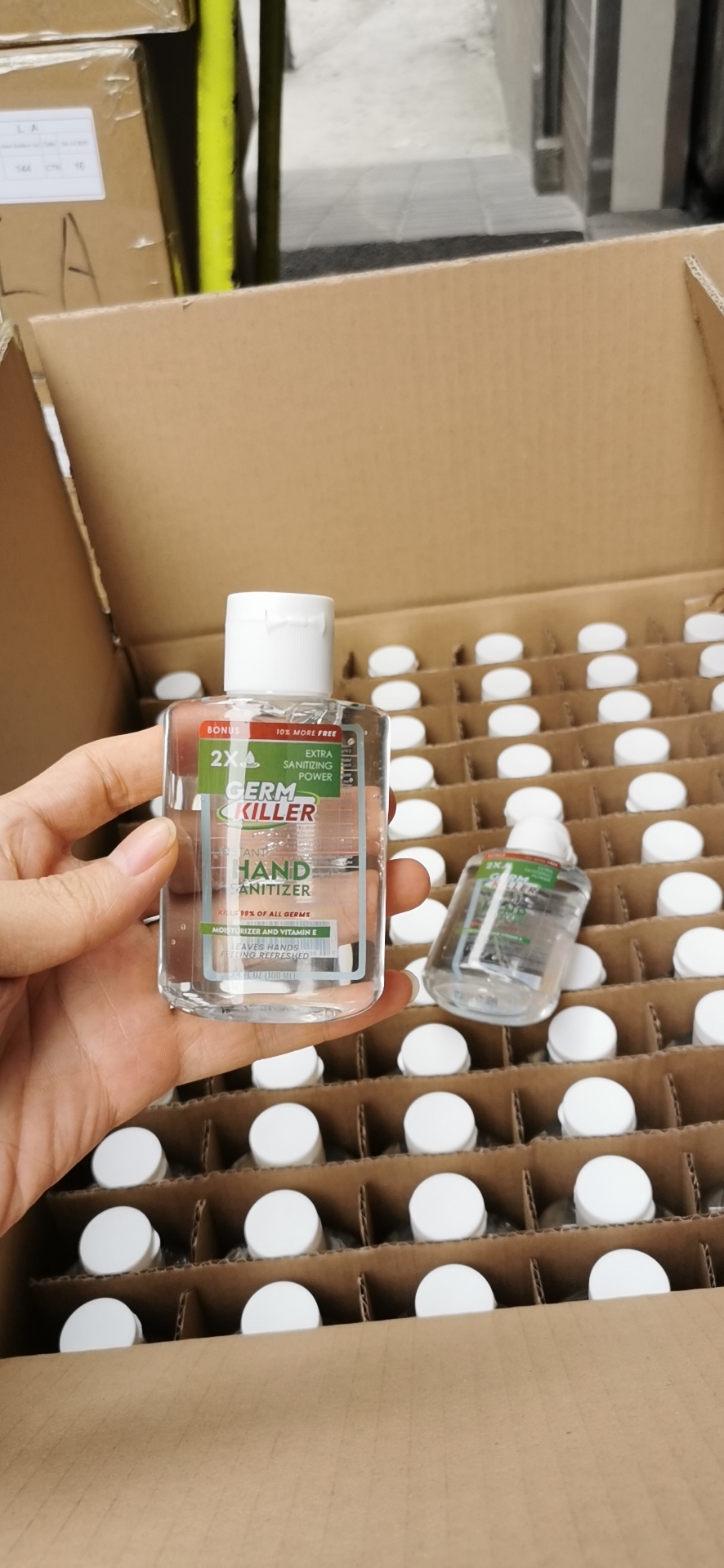 DRUG LABEL: Hand Sanitizer
NDC: 83029-201 | Form: GEL
Manufacturer: AMERICAN RAVEN
Category: otc | Type: HUMAN OTC DRUG LABEL
Date: 20241129

ACTIVE INGREDIENTS: ALCOHOL 68 g/112 mL
INACTIVE INGREDIENTS: WATER 68 g/112 mL

Hand Sanitizer

INDICATIONS AND USAGE

- Keep away from Children
- Apply on the hands only

DOSAGE AND ADMINISTRATION

- Use hand sanitizer if you can't use soap and water.
- Coat your palms and fingers.
- Rub in thoroughly for 20 seconds.
- Store in a cool, dry location.
- Keep out of children's reach

WARNINGS

- Store in a cool, dry location.
- Keep out of children's reach.
- Do not Ingest

INACTIVE INGREDIENT

- Emollients (e.g., glycerin, Aloe Vera): help moisturize skin.
- Polyacrylate (e.g., sodium polyacrylate): helps to thicken and stabilizes the ingredients.
- Color
- Fragrance: helps improve the scent.
- Water: carrier ingredient for the other active and inactive ingredients

Keep out of reach of Children

PURPOSE

This product is intended to be used to disinfect the hands when soap and water are not available, and are left on and not rinsed off with water.

ACTIVE INGREDIENT

70% Ethyl alcohol

PACKAGE LABEL

image attached